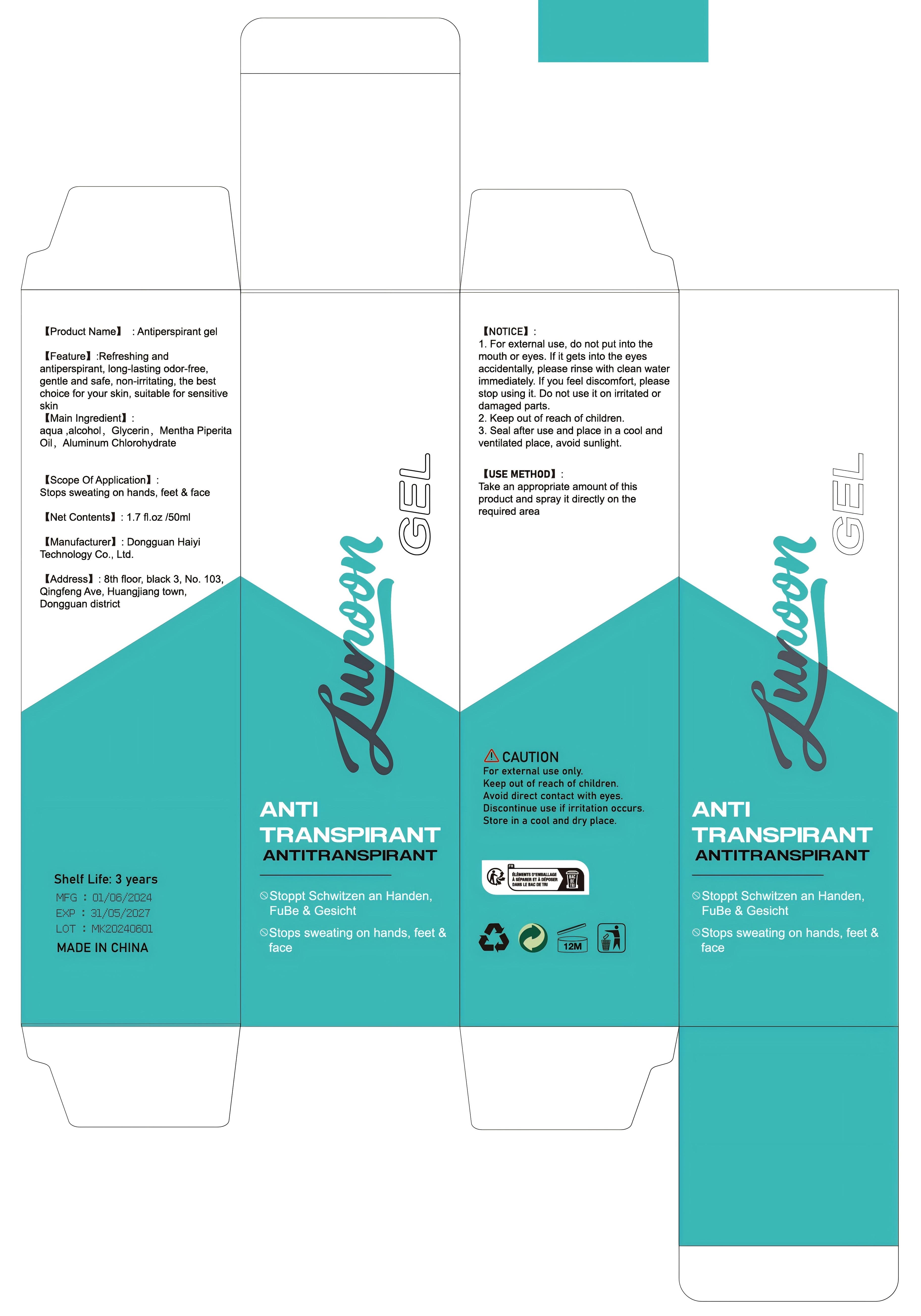 DRUG LABEL: Antiperspirant gel
NDC: 84732-052 | Form: GEL
Manufacturer: Dongguan Haiyi Technology Co.,Ltd.
Category: otc | Type: HUMAN OTC DRUG LABEL
Date: 20241017

ACTIVE INGREDIENTS: ALUMINUM CHLOROHYDRATE 1 mg/100 mL
INACTIVE INGREDIENTS: WATER; ALCOHOL; GLYCERIN; PEPPERMINT OIL

Active ingredient

Aluminum Chlorohydrate

Inactive ingredient

aqua ,alcohol, Glycerin, Mentha Piperita Oil

Purpose section

Refreshing and antiperspirant, long-lasting odor-free,gentle and safe, non-irritating, the bestchoice for your skin, suitable for sensitive skin

Warning

1. For external use, do not put into themouth or eyes. lf it gets into the eyesaccidentally, please rinse with clean waterimmediately. lf you feel discomfort, pleasestop using it. Do not use it on irritated ordamaged parts.

2. Keep out of reach of children.

3. Seal after use and place in a cool andventilated place, avoid sunlight.

stop use

This product may cause allergic reactions in as mall number of people.
lf you experience any discomfort,please stop using it immediately.

not use

Not suitable for use by children, pregnantor breast feeding people.

OUT OF CHILDREN

KEEP THE PRODUCT OUT OF REACH OF CHILDREN to

HOW TO USE

Take an appropriate amount of this product and spray it directly on the required area

Dosage

take an appropriateamount,Use 2-3 times a week